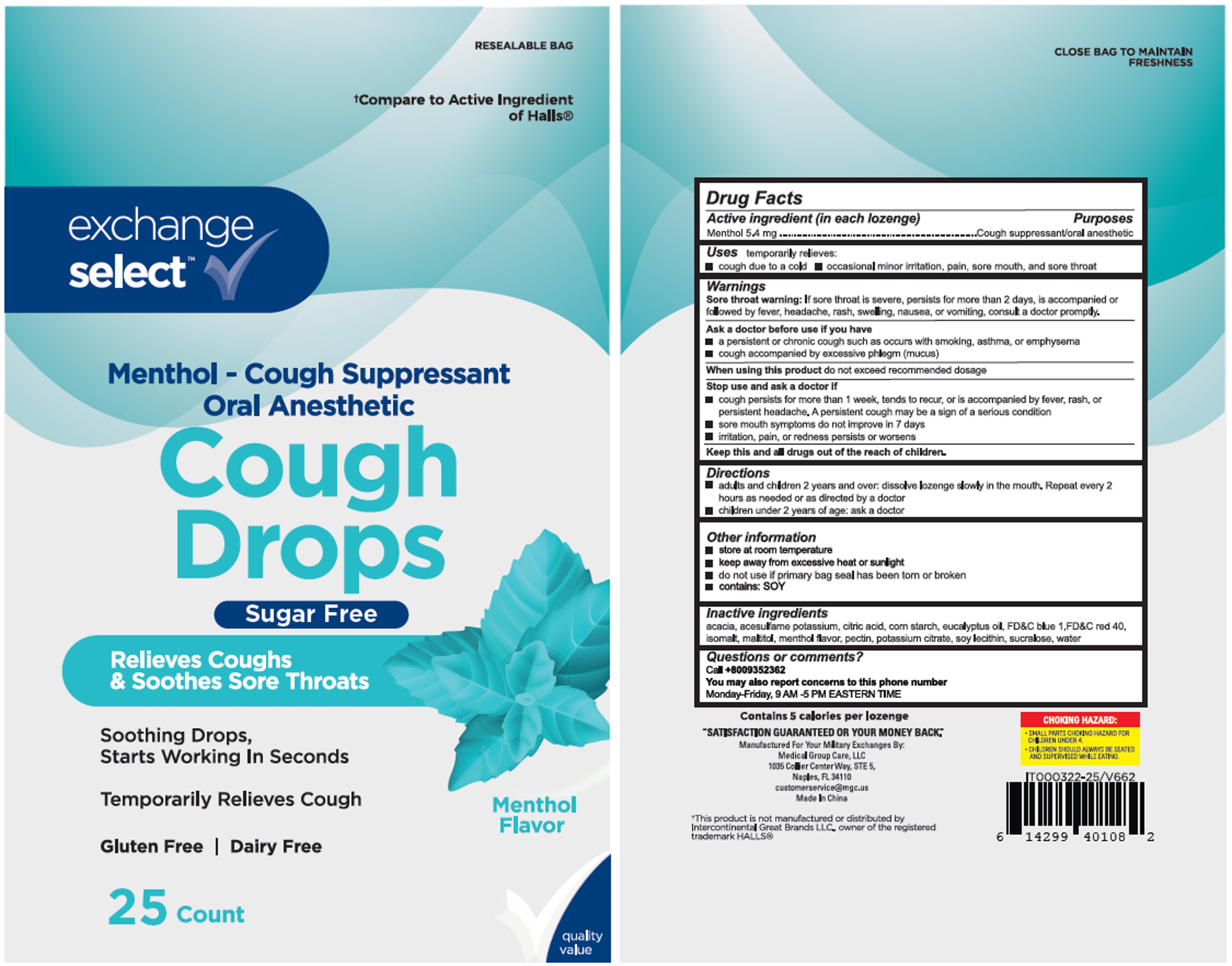 DRUG LABEL: Exchange Select Cough Drops
NDC: 55301-584 | Form: LOZENGE
Manufacturer: Army & Air Force Exchange Service
Category: otc | Type: HUMAN OTC DRUG LABEL
Date: 20250620

ACTIVE INGREDIENTS: MENTHOL 5.4 mg/1 1
INACTIVE INGREDIENTS: STARCH, CORN; PECTIN; LECITHIN, SOYBEAN; SUCRALOSE; WATER; FD&C BLUE NO. 1; FD&C RED NO. 40; ACESULFAME POTASSIUM; ISOMALT; EUCALYPTUS OIL; ACACIA; CITRIC ACID MONOHYDRATE; POTASSIUM CITRATE; MALTITOL

AAFES Cough Drops Menthol Sugar-Free 25

Active Ingredient(s)

Menthol 5.4 mg

Purpose

Purposes cough suppressant, oral anesthetic

Use

temporary relieves:

- cough due to a cold
- occasional minor irritation, pain, sore mouth, and sore throat

Warnings

Sore throat warning: If sore throat is severe, persists for more than 2 days, or is accompanied or followed by fever, headache, rash, swelling, nausea, or vomiting, consult a doctor promptly.

Ask a doctor before use if you have: ■ persistent or chronic cough such as occurs with smoking, asthma, or emphysema ■ cough accompanied by excessive phlegm (mucus).

Stop use and ask a doctor if :

- cough persists for more than 1 week, tends to recur, or is accompanied by fever, rash, or persistent headache (a persistent cough may be a sign of a serious condition)
- sore mouth symptoms don’t improve in 7 days
- irritation, pain, or redness persists or worsens

When using this product:
Do not exceed recommended dosage.

Keep out of reach of children.

Directions

- Adults and children 2 years and over: dissolve lozenge slowly in mouth. Repeat every 2 hours as needed or as directed by a doctor.
- Children under 2 years: ask a doctor.

Other information

- Store at room temperature
- Keep away from excessive heat or sunlight
- Do not use if primary bag seal has been torn or broken
- Contains: SOY

Inactive ingredients

acacia, acesulfame potassium, citric acid, corn starch, eucalyptus oil, FD&C blue 1, FD&C red 40, isomalt, maltitol, menthol flavor, pectin, potassium citrate, soy lecithin, sucralose, water

QUESTIONS

Call +8009352362
Available Monday–Friday, 9 AM–5 PM Eastern Time